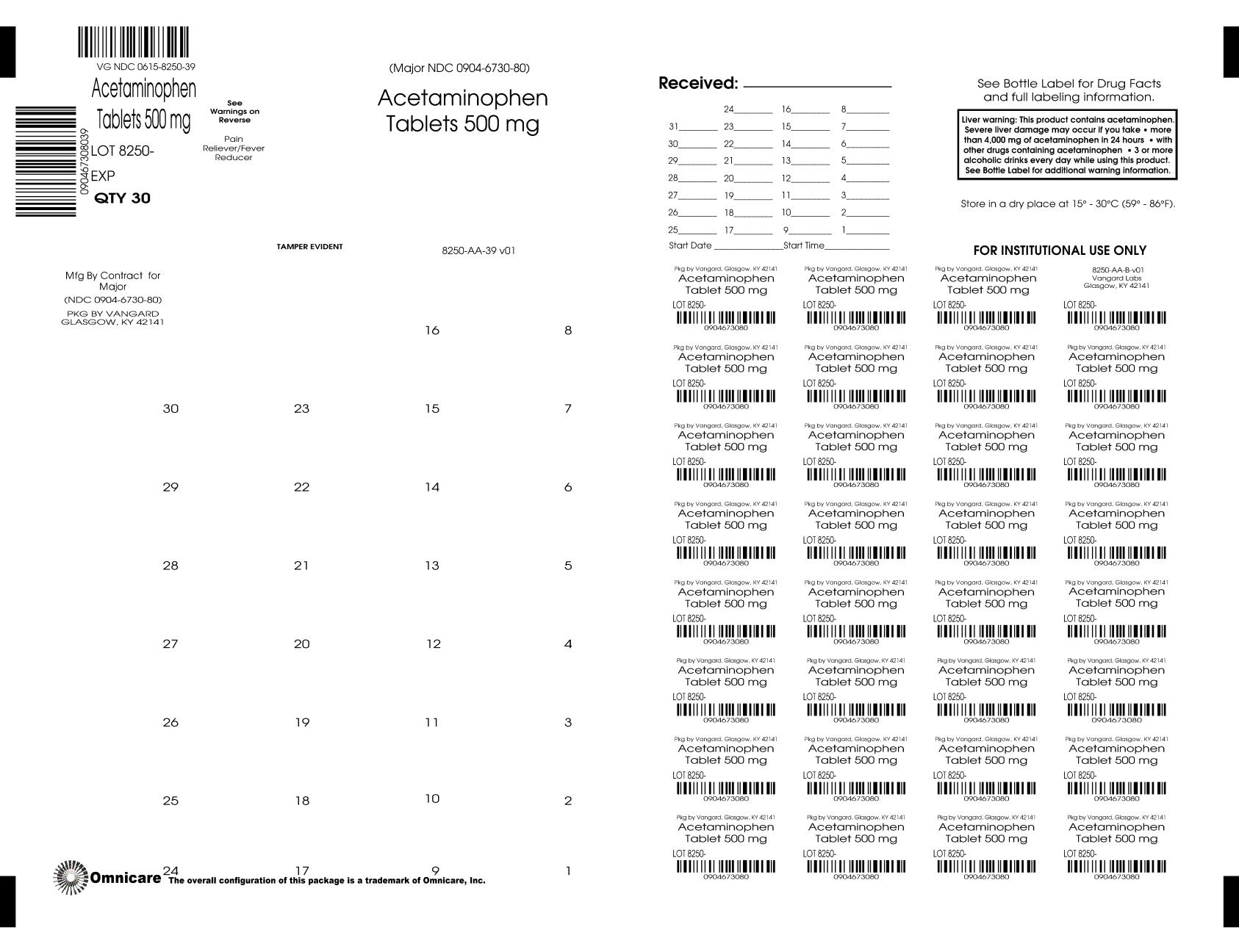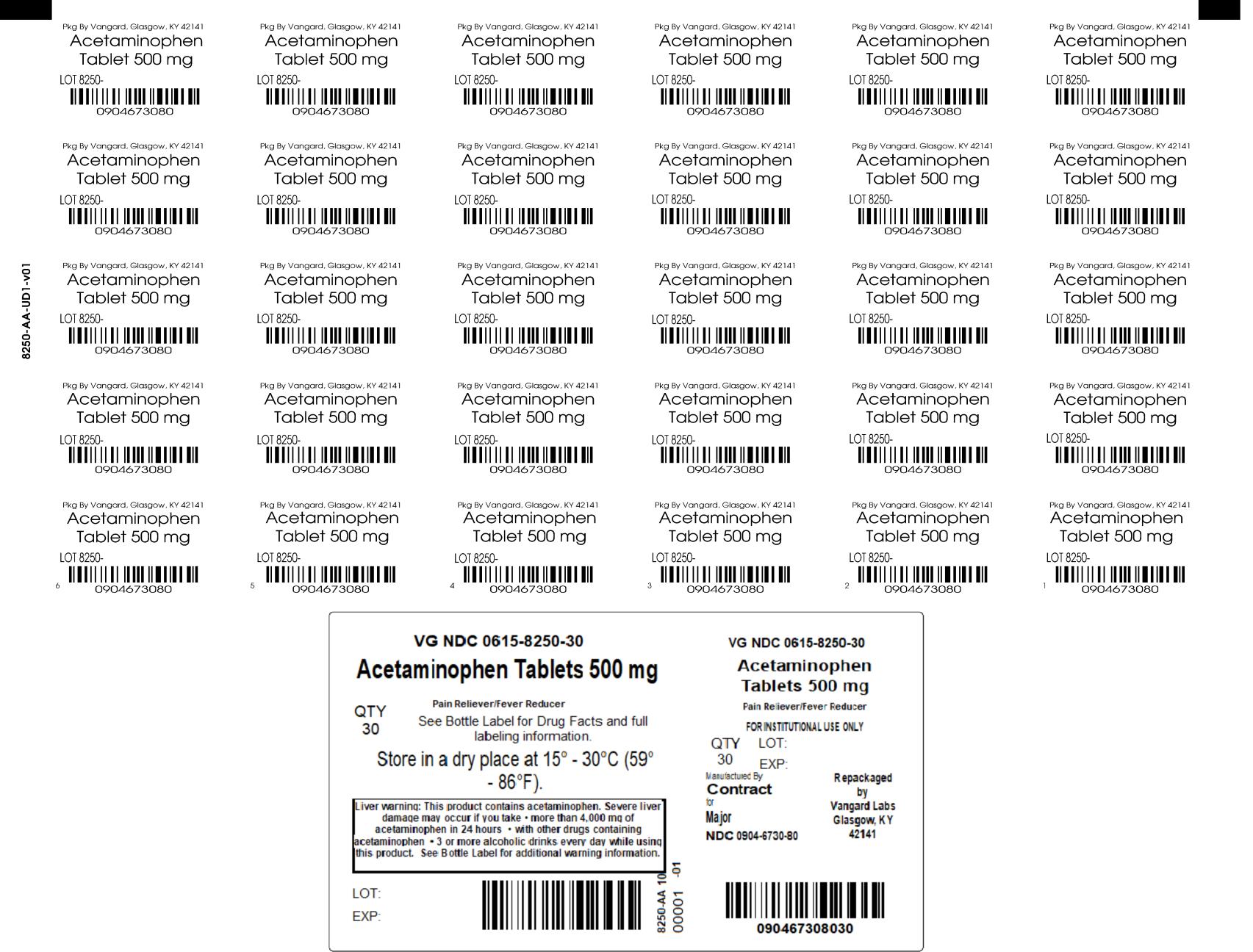 DRUG LABEL: Acetaminophen
NDC: 0615-8250 | Form: TABLET
Manufacturer: NCS HealthCare of KY, LLC dba Vangard Labs
Category: otc | Type: HUMAN OTC DRUG LABEL
Date: 20251117

ACTIVE INGREDIENTS: ACETAMINOPHEN 500 mg/1 1
INACTIVE INGREDIENTS: STARCH, CORN; STEARIC ACID; POVIDONE K30; SODIUM STARCH GLYCOLATE TYPE A POTATO

Acetaminophen Tabs 8250

Drug Facts

Active Ingredient (in each tablet)

Acetaminophen 500 mg

Purpose

Pain reliever/ Fever reducer

Uses

Temporarily reduces fever and relieves minor aches and pains due to:

- headache
- muscular aches
- the common cold
- toothache
- backache
- minor pain of arthritis
- premenstrual and menstrual cramps

Warnings

Liver warning: This product contains acetaminophen. Severe liver damage may occur if you take

- more than 4,000 mg of acetaminophen in 24 hours
- with other drugs containing acetaminophen
- 3 or more alcoholic drinks every day while using this product

Allergy alert: acetaminophen may cause severe skin reactions. Symptoms may include: • skin reddening • blisters • rash.

If a skin reaction occurs, stop use and seek medical help right away.

Do not use

- with any other drug containing acetaminophen (prescription or nonprescription). If you are not sure whether a drug contains acetaminophen, ask a doctor or pharmacist.
- if you are allergic to acetaminophen or any of the inactive ingredients in this product

Ask a doctor before use if you have liver disease

Ask a doctor or pharmacist before use if you are taking the blood thinning drug warfarin

Stop use and ask a doctor if

- pain gets worse or lasts more than 10 days
- fever gets worse or lasts more than 3 days
- new symptoms occur
- redness or swelling is present

These could be signs of a serious condition.

PREGNANCY OR BREAST FEEDING

If pregnant or breast-feeding, ask a health professional before use.

Keep out of reach of children.

OVERDOSAGE

Overdose warning: In case of overdose, get medical help or contact a Poison Control Center right away. (1-800-222-1222) Quick medical attention is critical for adults as well as for children even if you do not notice any signs or symptoms.

Directions

- do not take more than directed (see overdose warning)

adults and children 12 years and over:

• take 2 tablets every 6 hours while symptoms last

• do not take more than 6 tablets in 24 hours, unless directed by a doctor

• do not take for more than 10 days unless directed by a doctor

children under 12 years: ask a doctor

Other Information

store in a dry place at 15° – 30°C (59° – 86°F).

Inactive ingredients

Povidone, pregelatinized starch, sodium starch glycolate, stearic acid

Questions or comments?

Call 1-800-231-4670

TAMPER EVIDENT: DO NOT USE IF IMPRINTED SAFETY SEAL UNDER CAP IS BROKEN OR MISSING

Distributed By:

MAJOR® PHARMACEUTICALS
Indianapolis, IN 46268

*This product is not manufactured or distributed by Kenvue Inc., owner of the registered trademark Tylenol®.